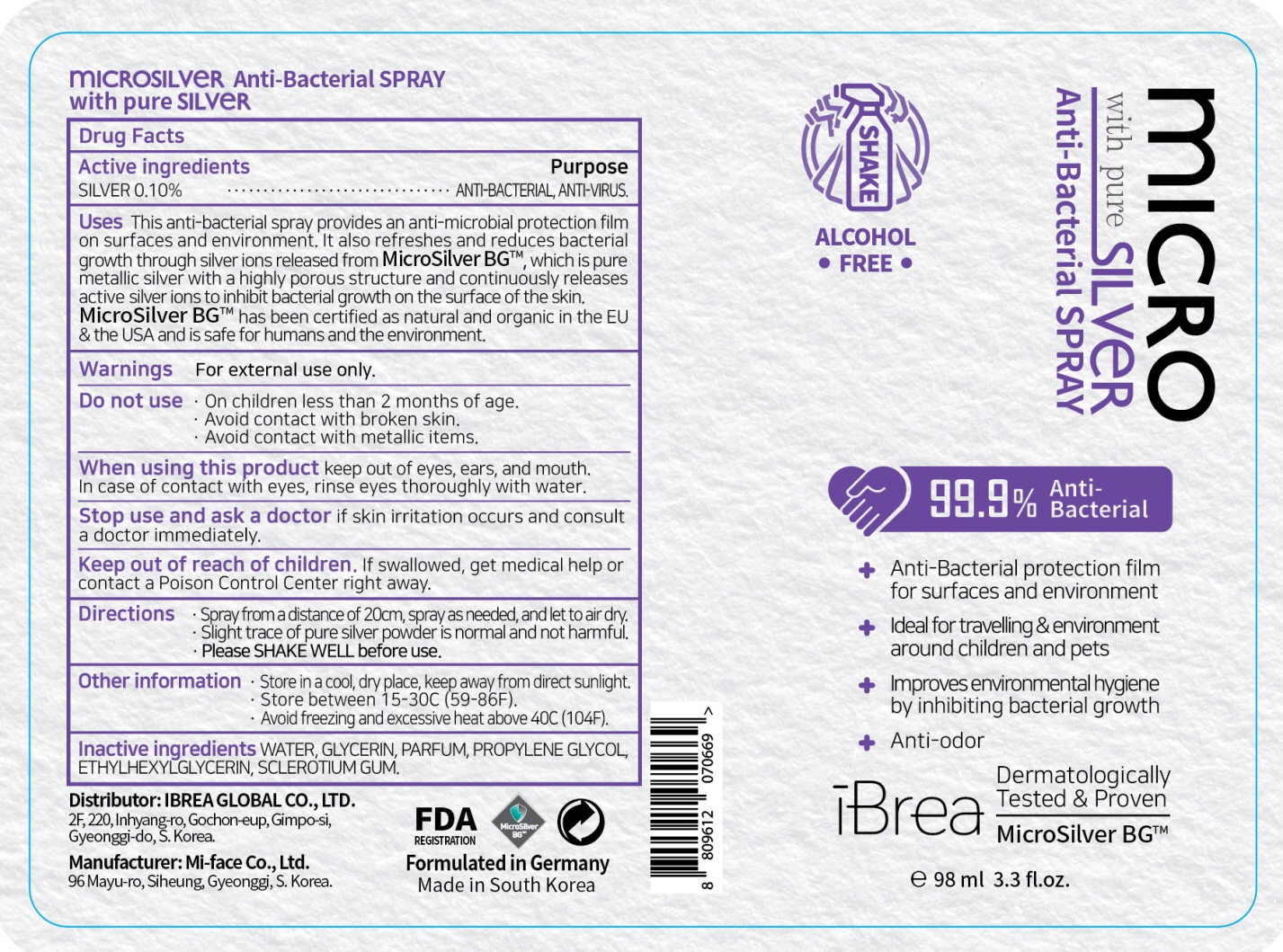 DRUG LABEL: iBrea Micro Silver Anti Bacterial With Pure Silver
NDC: 78030-040 | Form: SPRAY
Manufacturer: IBREA GLOBAL CO.,LTD.
Category: otc | Type: HUMAN OTC DRUG LABEL
Date: 20200709

ACTIVE INGREDIENTS: SILVER 0.098 g/98 mL
INACTIVE INGREDIENTS: Water; Glycerin; PROPYLENE GLYCOL; ETHYLHEXYLGLYCERIN; BETASIZOFIRAN

ACTIVE INGREDIENT

SILVER 0.10%

INACTIVE INGREDIENTS

WATER, GLYCERIN, PARFUM, PROPYLENE GLYCOL, ETHYLHEXYLGLYCERIN, SCLEROTIUM GUM.

PURPOSE

ANTI-BACTERIAL, ANTI-VIRUS.

WARNINGS

For external use only.
--------------------------------------------------------------------------------------------------------
Do not use
• On children less than 2 months of age.
• Avoid contact with broken skin.
• Avoid contact with metallic items.
--------------------------------------------------------------------------------------------------------
When using this product keep out of eyes, ears, and mouth. In case of contact with eyes, rinse eyes thoroughly with water.
--------------------------------------------------------------------------------------------------------
Stop use and ask a doctor if skin irritation occurs and consult a doctor immediately.

KEEP OUT OF REACH OF CHILDREN

If swallowed, get medical help or contact a Poison Control Center right away.

Uses

This anti-bacterial spray provides an anti-microbial protection film on surfaces and environment. It also refreshes and reduces bacterial growth through silver ions released from MicroSilver BG™, which is pure metallic silver with a highly porous structure and continuously releases active silver ions to inhibit bacterial growth on the surface of the skin.
MicroSilver BG™ has been certified as natural and organic in the EU & the USA and is safe for humans and the environment.

Directions

• Spray from a distance of 20cm, spray as needed, and let to air dry.
• Slight trace of pure silver powder is normal and not harmful.
• Please SHAKE WELL before use.

Other information

• Store in a cool, dry place, keep away from direct sunlight.
• Store between 15-30C (59-86F).
• Avoid freezing and excessive heat above 40C (104F).